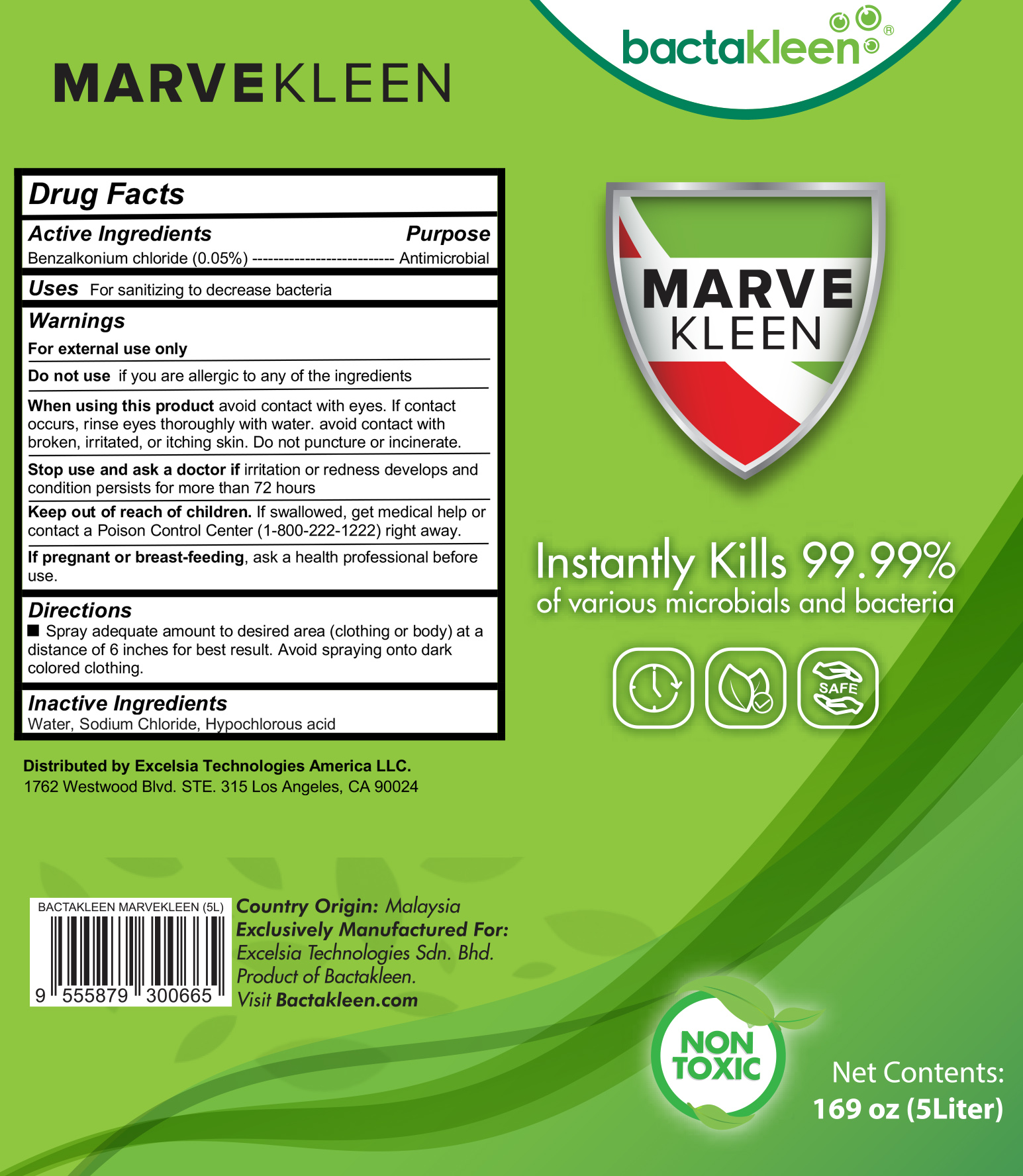 DRUG LABEL: Bactakleen Marvekleen
NDC: 73215-109 | Form: LIQUID
Manufacturer: Excelsia Technologies Sdn Bhd
Category: otc | Type: HUMAN OTC DRUG LABEL
Date: 20200423

ACTIVE INGREDIENTS: BENZALKONIUM CHLORIDE 0.05 g/100 mL
INACTIVE INGREDIENTS: HYPOCHLOROUS ACID; WATER; SODIUM CHLORIDE

Bactakleen Marvekleen

Active Ingredients

Benzalkonium chloride (0.05%)

Purpose

Antibacterial

Keep out of reach of children

If swallowed, get medical help or contact a Poison Control Center (1-800-222-1222) right away.

Uses

For sanitizing to decrease bacteria

Warnings

For external use only

Do not use if you are allergic to any of the ingredients

When using this product avoid contact with eyes. If contact occurs, rinse eyes thoroughly with water. avoid contact with broken, irritated, or itching skin. Do not puncture or incinerate.

Stop use and ask a doctor if irritation or redness develops and condition persists for more than 72 hours

If pregnant or breast-feeding, ask a health professional before use.

Directions

Spray adequate amount to desired area (clothing or body) at a distance of 6 inches for best result. Avoid spraying onto dark colored clothing.

Inactive Ingredients

Water, Sodium Chloride, Hypochlorous acid